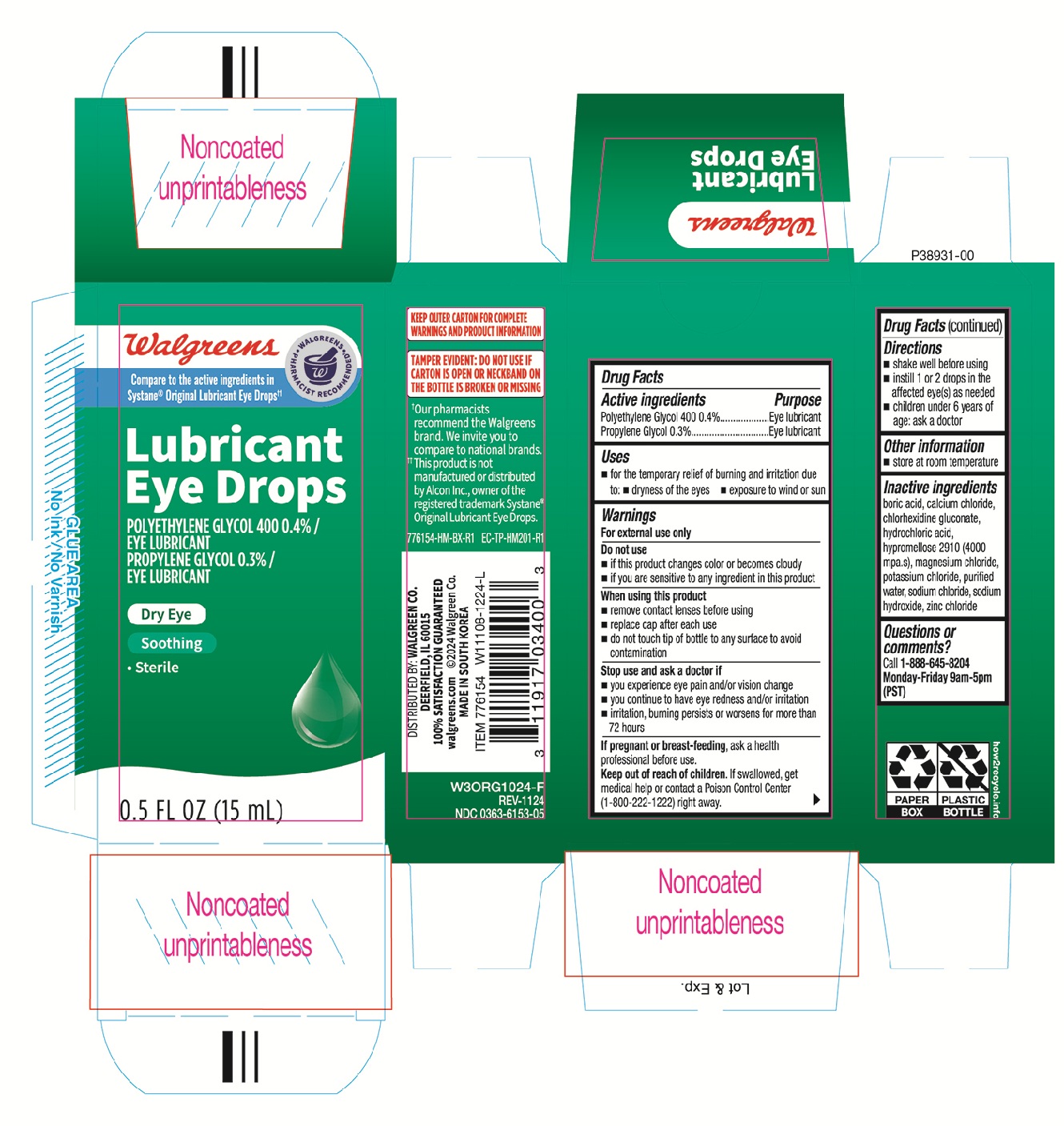 DRUG LABEL: Walgreens Lubricant
NDC: 0363-6153 | Form: SOLUTION/ DROPS
Manufacturer: Walgreens
Category: otc | Type: HUMAN OTC DRUG LABEL
Date: 20251219

ACTIVE INGREDIENTS: PROPYLENE GLYCOL 3 mg/1 mL; POLYETHYLENE GLYCOL 400 4 mg/1 mL
INACTIVE INGREDIENTS: SODIUM HYDROXIDE; POTASSIUM CHLORIDE; BORIC ACID; CHLORHEXIDINE GLUCONATE; CALCIUM CHLORIDE; HYPROMELLOSE 2910 (4000 MPA.S); WATER; SODIUM CHLORIDE; HYDROCHLORIC ACID; ZINC CHLORIDE; MAGNESIUM CHLORIDE

Walgreens Soothing Lubricant 776154 Eye Drops 0.5oz (NBE Systane Original)

Active Ingredients Purpose

Polyethylene Glycol 400 0.4%.....................Eye lubricant

Propylene Glycol 0.3%................................Eye lubricant

Uses

- for the temporary relief of burning and irritation due to:
- dryness of the eyes
- exposure to wind or sun

Warnings

For exnternal use only

Do not use

- if this product changes color or becomes cloudy
- if you are sensitive to any ingredient in this product

When using this product

- remove contact lenses before using
- replace cap after each use
- do not touch tip of bottle to any surface to avoid contamination

Stop use and ask a doctor if

- you experience eye pain and/or vision change
- you continue to have eye redness and/or irritation
- irritation, burning persists or worsens for more than 72 hours

PREGNANCY OR BREAST FEEDING

If pregnant or breast-feeding, ask a health professional before use.

Keep out of reach of children. If swallowed, get medical help or contact a Poison Control Center (1-800-222-1222) right away.

Directions

- shake well before using
- instill 1 or 2 drops in the affected eye(s) as needed
- children under 6 years of age: ask a doctor

Other information

- store at room temperature

Inactive ingredients

boric acid, calcium chloride, chlorhexidine gluconate, hydrochloric acid, hypromellose 2910 (4000 mpa.s), magnesium chloride, potassium chloride, purified water, sodium chloride, sodium hydroxide, zinc chloride

DOSAGE AND ADMINISTRATION

Distributed by:

Walgreen Co.

Deerfield, IL 60015

Made in South Korea